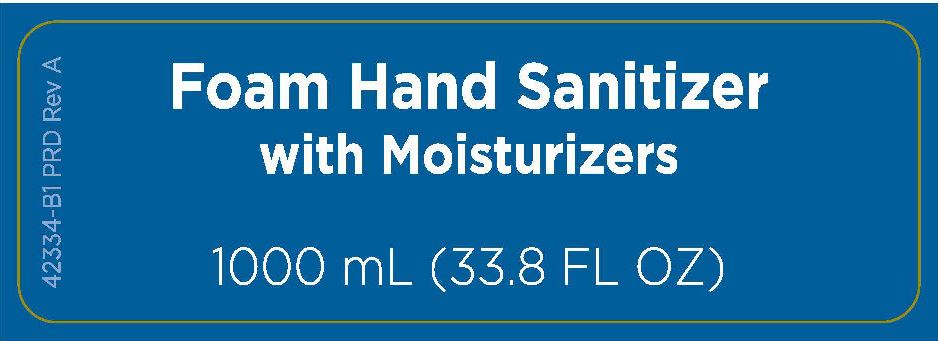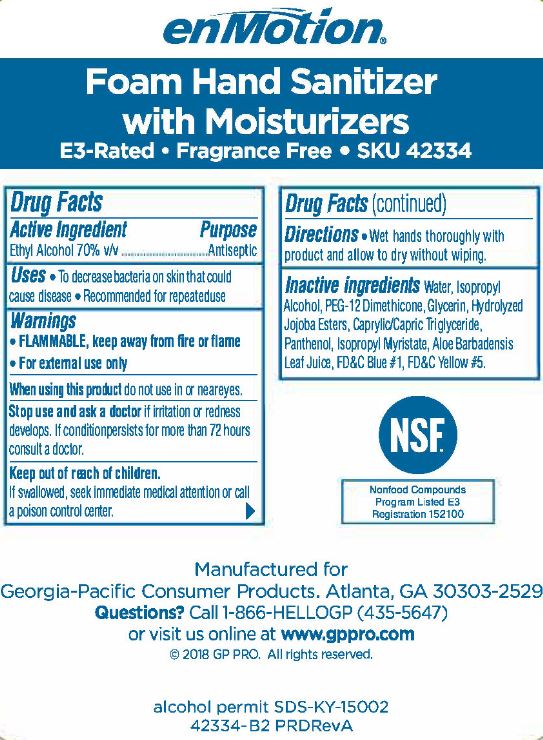 DRUG LABEL: EnMotion Foam Hand Sanitizer
NDC: 54622-120 | Form: LIQUID
Manufacturer: Georgia-Pacific Consumer Products LP
Category: otc | Type: HUMAN OTC DRUG LABEL
Date: 20250123

ACTIVE INGREDIENTS: ALCOHOL 70 mL/100 mL
INACTIVE INGREDIENTS: WATER; ISOPROPYL ALCOHOL; PEG-12 DIMETHICONE (300 CST); GLYCERIN; POTASSIUM HYDROLYZED JOJOBA ESTERS; PANTHENOL; ISOPROPYL MYRISTATE; ALOE VERA LEAF; FD&C BLUE NO. 1; FD&C YELLOW NO. 5; MEDIUM-CHAIN TRIGLYCERIDES

enMotion E3 Rated-Foam Hand Sanitizer 54622-120

Drug Facts

Active ingredient

Ethyl Alcohol 70% v/v

Purpose

Antiseptic

Uses

- To decrease bacteria on skin that could cause disease
- Recommended for repeated use

Warnings

- FLAMMABLE, keep away from fire or flame
- For external use only

WHEN USING

When using this productdo not use in or near eyes.

Stop use and ask doctorif irritation or redness develops. If condition persists for more than 72 hours consult a doctor.

Keep out of reach of children.If swallowed, seek immediate medical attention or call a poison control center.

Directions

Wet hands thoroughly with product and allow to dry without wiping.

INACTIVE INGREDIENT

Inactive ingredientsWater, Isopropyl Alcohol, PEG-12 Dimethicone, Glycerin, Hydrolyzed Jojoba Esters, Caprylic/Capric Triglyceride, Panthenol, Isopropyl Myristate, Aloe Barbadensis Leaf Juice, FD&C Blue #1, FD&C Yellow #5

enMotion

Foam Hand Sanitizer with Moisturizers

E3-Rated Frgrance Free SKU 42334

NSF

NonfoodCompounds

Program Listed E3

Registration 152100

Manufactured for

Georgia-Pacific Consumer Products. Atlanta, GA 30303-2529

Questions?Call 1-866-HELLOGP (435-5647)

or visit us online at www.gppro.com

© 2018 GP PRO. All rights reserved.

alcohol permit SDS-KY-15002

42334-B2 PRDRevA

PACKAGE LABEL

Foam Hand Sanitizer

with Moisturizers

1000 mL (33.8 FL OZ)